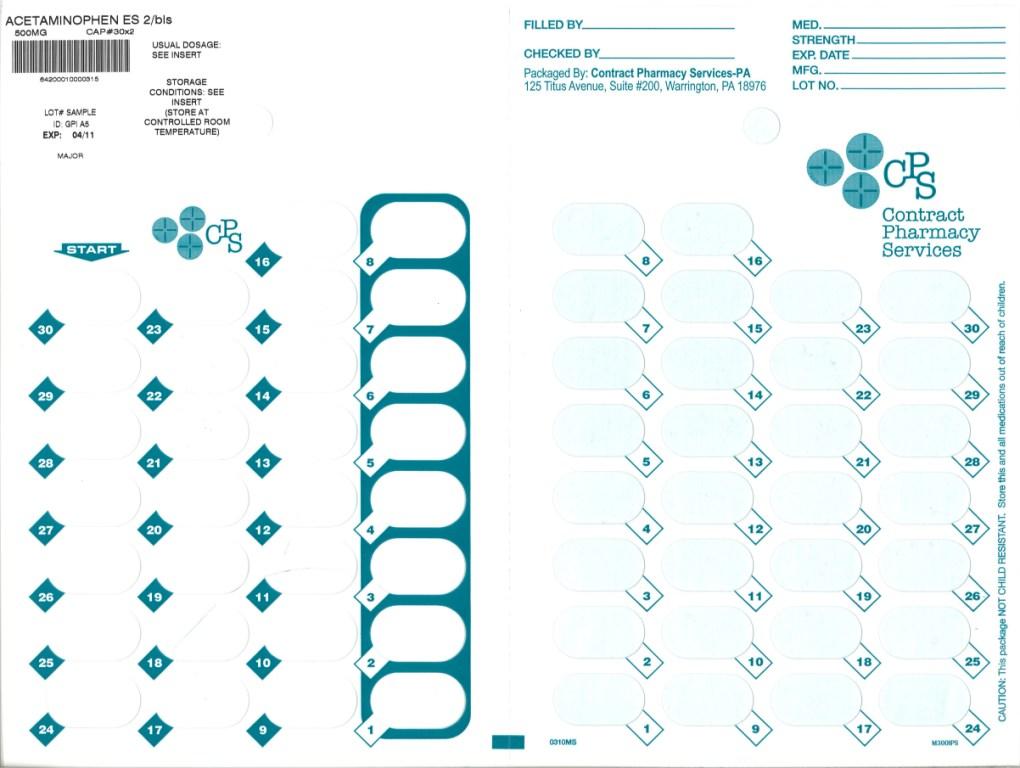 DRUG LABEL: Extra Strength Acetaminophen
NDC: 67046-026 | Form: TABLET
Manufacturer: Contract Pharmacy Services-PA
Category: otc | Type: HUMAN OTC DRUG LABEL
Date: 20100730

ACTIVE INGREDIENTS: ACETAMINOPHEN 500 mg/1 1

Extra Strength Acetaminophen Tablets

ACTIVE INGREDIENT (IN EACH CAPLET)

Acetaminophen Caplets, 500 mg

PURPOSE

Pain reliever/fever reducer

USES

- temporarily reduces fever
- temporarily relieves minor aches and pains due to:
  1. headache
  2. muscular aches
  3. the common cold
  4. minor pain of arthritis
  5. backache
  6. toothache
  7. premenstrual and menstrual cramps

WARNINGS

Liver warning: This product contains acetaminophen. Severe liver damage may occur if you take

- more than 8 tablets in 24 hours, which is the maximum daily amount
- with other drugs containing acetaminophen
- 3 or more alcoholic drinks every day while using this product

Do not use

- with any other drug containing acetaminophen (prescription or nonprescription). If you are not sure whether a drug contains acetaminophen, ask a doctor or pharmacist.
- if you are allergic to acetaminophen or any of the inactive ingredients in this product

Ask a doctor before use if you

have liver disease

Ask a doctor or pharmacist before use if

you are taking the blood thinning drug warfarin

Stop use and ask a doctor if

- pain gets worse or lasts more than 10 days
- fever gets worse or lasts more than 3 days
- new symptoms occur
- redness or swelling is present

These could be signs of a serious condition.

If pregnant or breast-feeding,

ask a health professional before use.

Keep out of reach of children.

Overdose warning: Taking more than the recommended dose (overdose) may cause liver damage. In case of overdose, get medical help or contact a Poison Control Center right away. (1-800-222-1222). Quick medical attention is critical for adults as well as for children even if you do not notice any signs or symptoms.

DIRECTIONS

adults and children; 12 years and over | - take 2 tablets every 4 to 6 hours while symptoms last - do not take more than 8 tablets in 24 hours - do not take for more than 10 days unless directed by a doctor
 | do not use adult Extra Strength product in children under 12 years of age; this will provide more than the recommended dose (overdose) and may cause liver damage

OTHER INFORMATION

store at 15° to 30°C (59° to 86°F)

INACTIVE INGREDIENTS

povidone, pregelatinized starch, stearic acid

QUESTIONS OR COMMENTS?

Distributed by: Major Pharmaceuticals, 31778 Enterprise Drive, Livonia, MI 48150, U.S.A.

call toll free 734-743-6000

Repackaged by:
Contract Pharmacy Services-PA
125 Titus Ave Suite 200
Warrington, PA 18976 USA

Original--08/2010--NJW

Package Label

500 mg Tablets